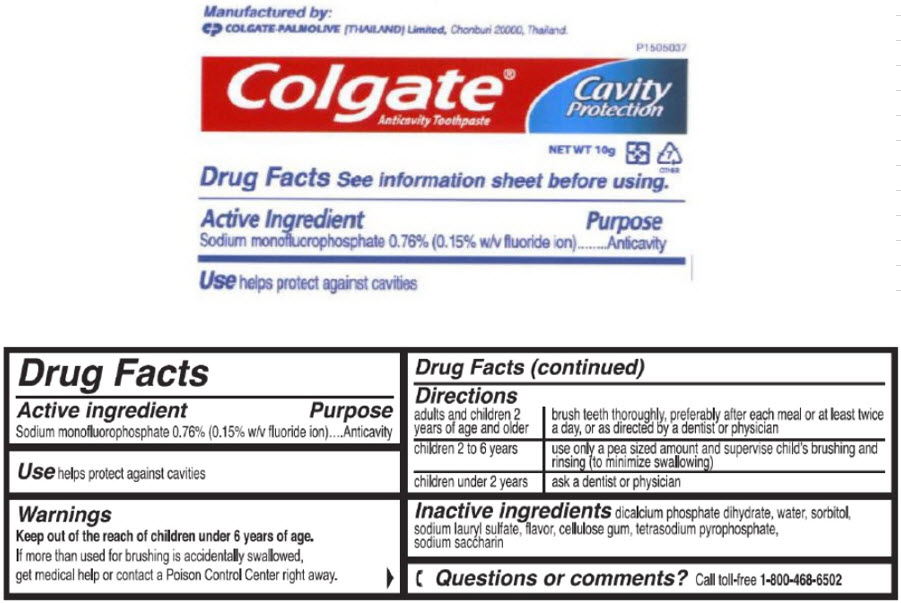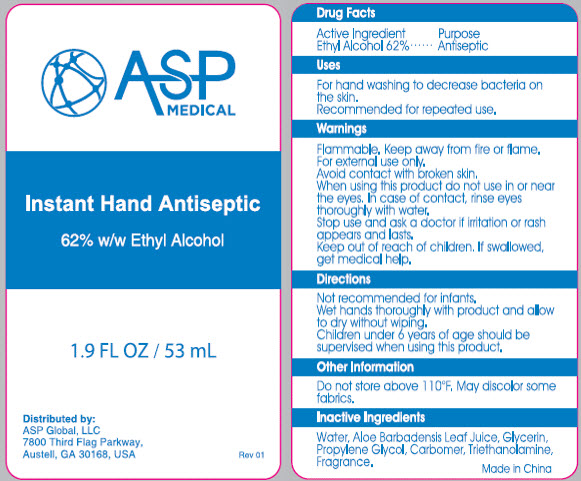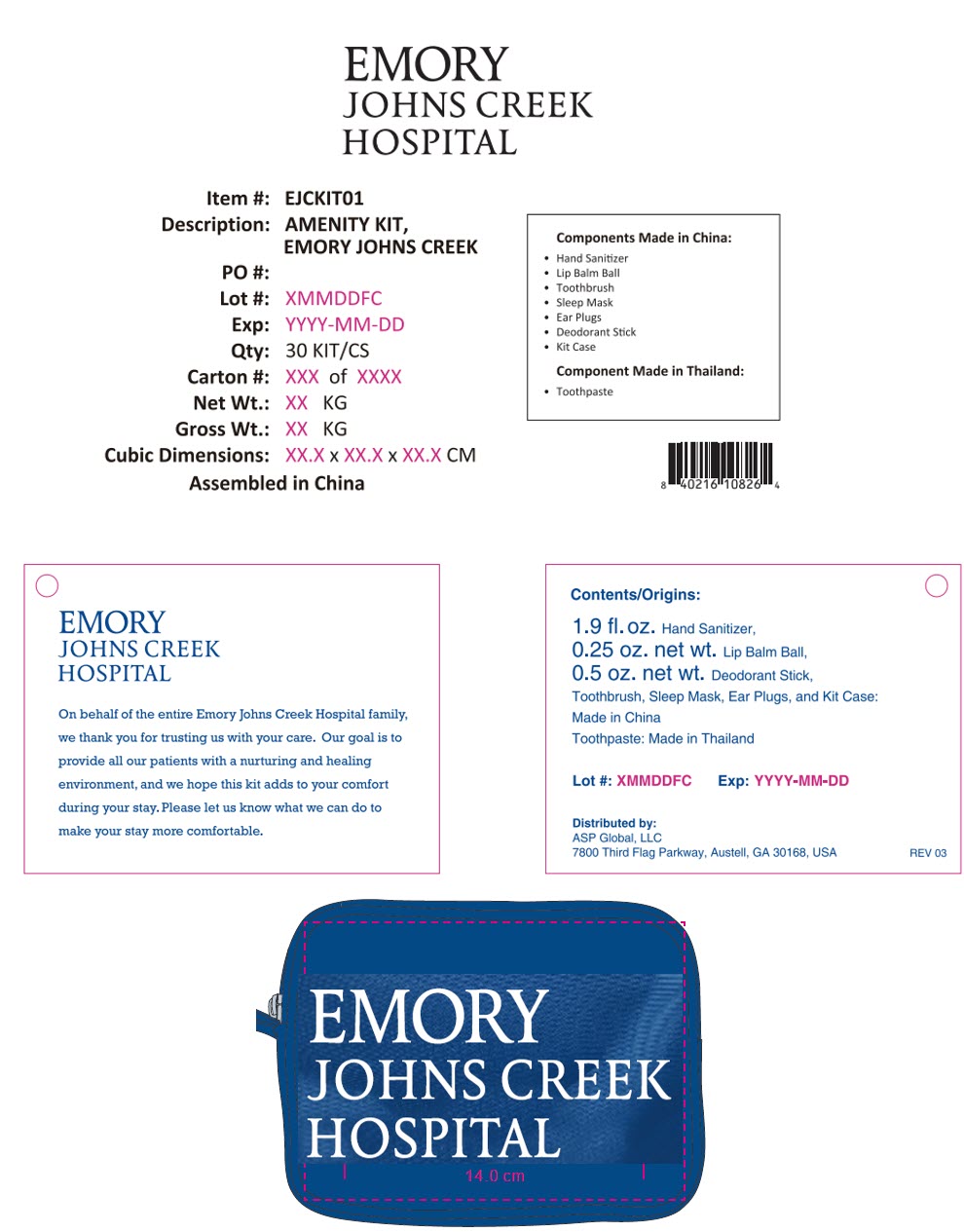 DRUG LABEL: Emory Johns Creek Amenity
NDC: 59448-700 | Form: KIT | Route: TOPICAL
Manufacturer: ASP Global
Category: otc | Type: HUMAN OTC DRUG LABEL
Date: 20241204

ACTIVE INGREDIENTS: ALCOHOL 62 mL/100 mL; SODIUM MONOFLUOROPHOSPHATE 7.6 mg/1 g
INACTIVE INGREDIENTS: WATER; ALOE VERA LEAF; GLYCERIN; PROPYLENE GLYCOL; CARBOMER INTERPOLYMER TYPE A (ALLYL SUCROSE CROSSLINKED); TROLAMINE; DIBASIC CALCIUM PHOSPHATE DIHYDRATE; WATER; SORBITOL; SODIUM LAURYL SULFATE; SODIUM PYROPHOSPHATE; SACCHARIN SODIUM

Emory Johns Creek Amenity Kit

Instant Hand Antiseptic

Drug Facts

Active Ingredient

Ethyl Alcohol 62%

Purpose

Antiseptic

Uses

For hand washing to decrease bacteria on the skin.

Recommended for repeated use.

Warnings

Flammable. Keep away from fire or flame.

For external use only.

Avoid contact with broken skin.

When using this product do not use in or near the eyes. In case of contact, rinse eyes thoroughly with water.

Stop use and ask a doctor if irritation or rash appears and lasts.

Keep out of reach of children. If swallowed, get medical help.

Directions

Not recommended for infants.

Wet hands thoroughly with product and allow to dry without wiping.

Children under 6 years of age should be supervised when using this product.

Other Information

Do not store above 110°F. May discolor some fabrics.

Inactive Ingredients

Water, Aloe Barbadensis Leaf Juice, Glycerin, Propylene Glycol, Carbomer, Triethanolamine, Fragrance.

Distributed by:
ASP Global, LLC
7800 Third Flag Parkway,
Austell, GA 30168, USA

Colgate® Anticavity Toothpaste

Drug Facts

Active ingredient

Sodium monofluorophosphate 0.76% (0.15% w/v fluoride ion)

Purpose

Anticavity

Use

helps protect against cavities

Warnings

KEEP OUT OF REACH OF CHILDREN

Keep out of the reach of children under 6 years of age.

If more than used for brushing is accidentally swallowed, get medical help or contact a Poison Control Center right away.

Directions

adults and children 2 years of age and older | brush teeth thoroughly, preferably after each meal or at least twice a day, or as directed by a dentist or physician
children 2 to 6 years | use only a pea sized amount and supervise child's brushing and rinsing (to minimize swallowing)
children under 2 years | ask a dentist or physician

Inactive ingredients

dicalcium phosphate dihydrate, water, sorbitol, sodium lauryl sulfate, flavor, cellulose gum, tetrasodium pyrophosphate, sodium saccharin

Questions or comments?

Call toll-free 1-800-468-6502

PRINCIPAL DISPLAY PANEL - 53 mL Bottle Label

ASP
MEDICAL

Instant Hand Antiseptic

62% w/w Ethyl Alcohol

1.9 FL OZ / 53 mL

Distributed by:
ASP Global, LLC
7800 Third Flag Parkway,
Austell, GA 30168, USA

Rev 01

PRINCIPAL DISPLAY PANEL - 10 g Tube Label

P1505037

Colgate®
Anticavity Toothpaste

Cavity
Protection

NET WT 10g

7
OTHER

PRINCIPAL DISPLAY PANEL - Kit Label

EMORY
JOHNS CREEK
HOSPITAL

Item #: EJCKIT01
Description: AMENITY KIT,
EMORY JOHNS CREEK
PO #:
Lot #: XMMDDFC
Exp: YYYY-MM-DD
Qty: 30 KIT/CS
Carton #: XXX of XXXX
Net Wt.: XX KG
Gross Wt.: XX KG
Cubic Dimensions: XX.X x XX.X x XX.X CM

Assembled in China

Components Made in China:

- Hand Sanitizer
- Lip Balm Ball
- Toothbrush
- Sleep Mask
- Ear Plugs
- Deodorant Stick
- Kit Case

Component Made in Thailand:

- Toothpaste

EMORY
JOHNS CREEK
HOSPITAL

On behalf of the entire Emory Johns Creek Hospital family,
we thank you for trusting us with your care. Our goal is to
provide all our patients with a nurturing and healing
environment, and we hope this kit adds to your comfort
during your stay. Please let us know what we can do to
make your stay more comfortable.

Contents/Origins:

1.9 fl. oz. Hand Sanitizer,
0.25 oz. net wt. Lip Balm Ball,
0.5 oz. net wt. Deodorant Stick,
Toothbrush, Sleep Mask, Ear Plugs, and Kit Case:
Made in China
Toothpaste: Made in Thailand

Lot #: XMMDDFC
Exp: YYYY-MM-DD

Distributed by:
ASP Global, LLC
7800 Third Flag Parkway, Austell, GA 30168, USA

REV 03

EMORY
JOHNS CREEK
HOSPITAL